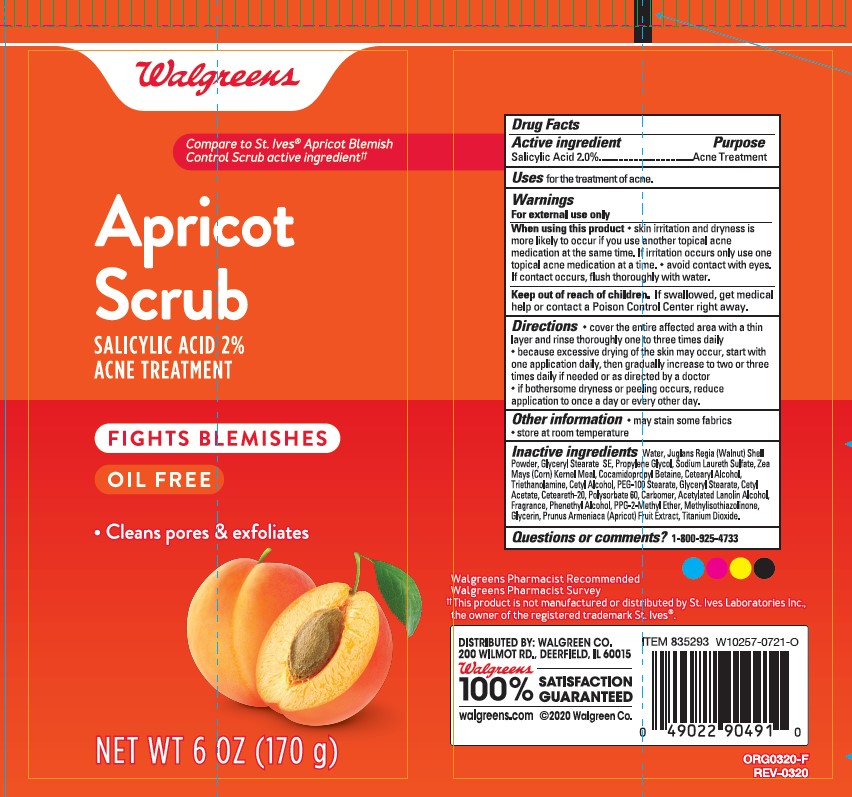 DRUG LABEL: WALGREENS APRICOT SCRUB ACNE TREATMENT
NDC: 0363-0951 | Form: EMULSION
Manufacturer: WALGREEN COMPANY
Category: otc | Type: HUMAN OTC DRUG LABEL
Date: 20241014

ACTIVE INGREDIENTS: SALICYLIC ACID 20 mg/1 g
INACTIVE INGREDIENTS: JUGLANS REGIA SHELL; CORN GRAIN; GLYCERIN; GLYCERYL STEARATE/PEG-100 STEARATE; POLYOXYL 20 CETOSTEARYL ETHER; CETYL ACETATE; ACETYLATED LANOLIN ALCOHOLS; POLYSORBATE 60; PPG-2 METHYL ETHER; APRICOT; WATER; CARBOMER HOMOPOLYMER TYPE B (ALLYL SUCROSE CROSSLINKED); TITANIUM DIOXIDE; COCAMIDOPROPYL BETAINE; PROPYLENE GLYCOL; SODIUM LAURETH SULFATE; GLYCERYL STEARATE SE; CETYL ALCOHOL; TROLAMINE; METHYLISOTHIAZOLINONE; PHENYLETHYL ALCOHOL; LINALOOL, (+/-)-; LIMONENE, (+/-)-; CETOSTEARYL ALCOHOL

WALGREENS APRICOT SCURB ACNE TREATMENT

Active ingredient

Salicylic Acid 2%

Purpose

Acne Treatment

Uses

for the treatment of acne.

Warnings

For external use only

When using this product

- skin irritation and dryness is more likely to occur if you use another topical acne medication at the same time. If irritation occurs only use one topical acne medication at a time.
- avoid contact with eyes. If contact occurs, flush thoroughly with water.

Keep out of reach of children.

If swallowed, get medical help or contact a Poison Control Center right away.

Directions

- cover the entire affected area with a thin layer and rinse thoroughly one to three times daily
- because excessive drying of the skin may occur, start with one application daily, then gradually increase to two or three times daily if needed or as directed by a doctor
- if bothersome dryness or peeling occurs, reduce application to once a day or every other day.

Other information

- may stain some fabrics
- store at room temperature

Inactive ingredients

water, juglans regia (walnut) shell powder, glyceryl stearate SE, propylene glycol, sodium laureth sulfate, zea mays (corn) kernel meal, cocamidopropyl betaine, cetearyl alcohol, triethanolamine, cetyl alcohol, PEG-100 stearate, glcyeryl stearate, cetyl acetate, ceteareth-20, polysorbate 60, carbomer, acetylated lanolin alcohol, fragrance (parfum), phenethyl alcohol, PPG-2-methyl ether, limonene, linalool, methylisothiazolinone, glycerin, prunus armeniaca (apricot) fruit extract, titanium dioxide (CI177891).